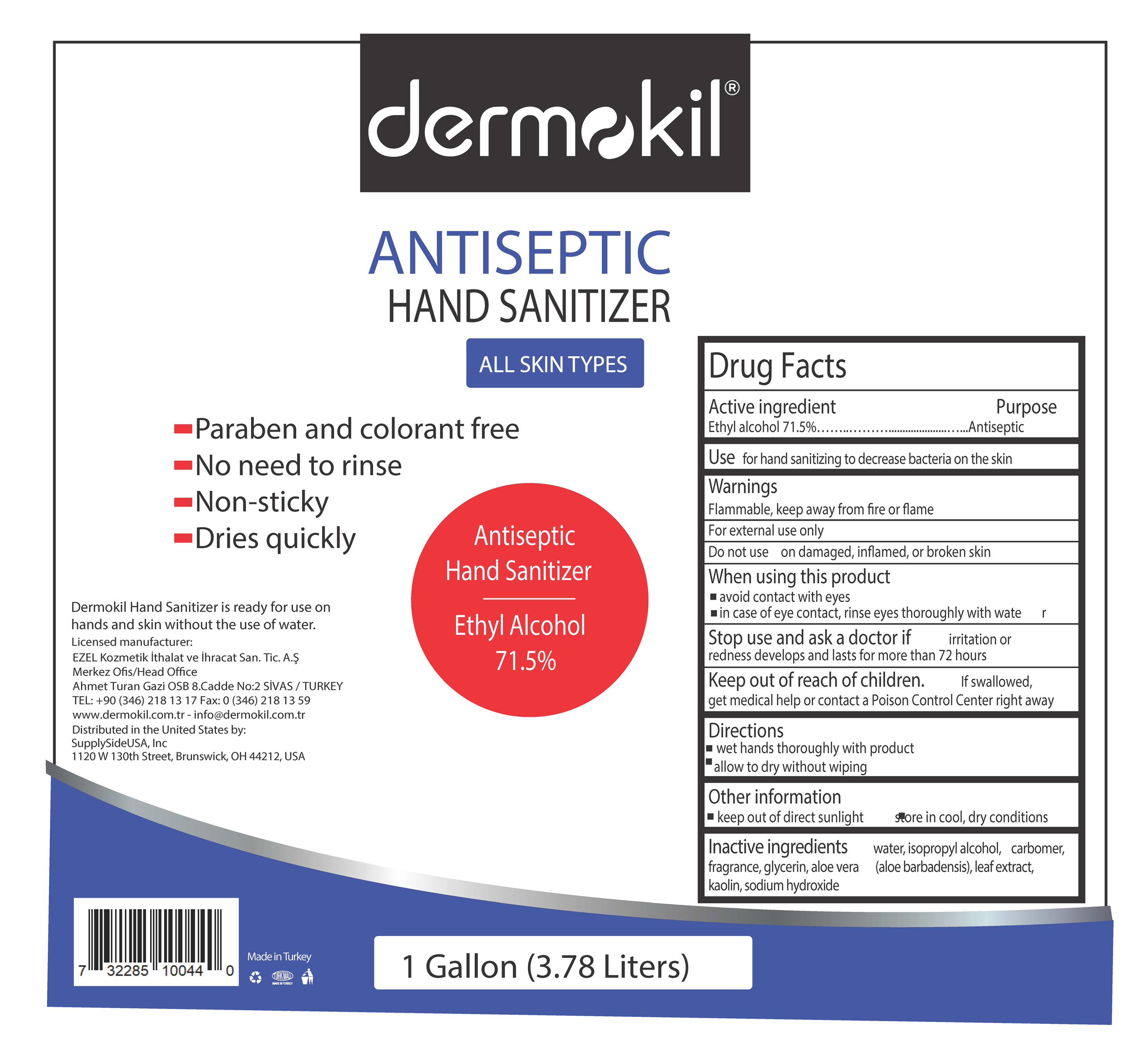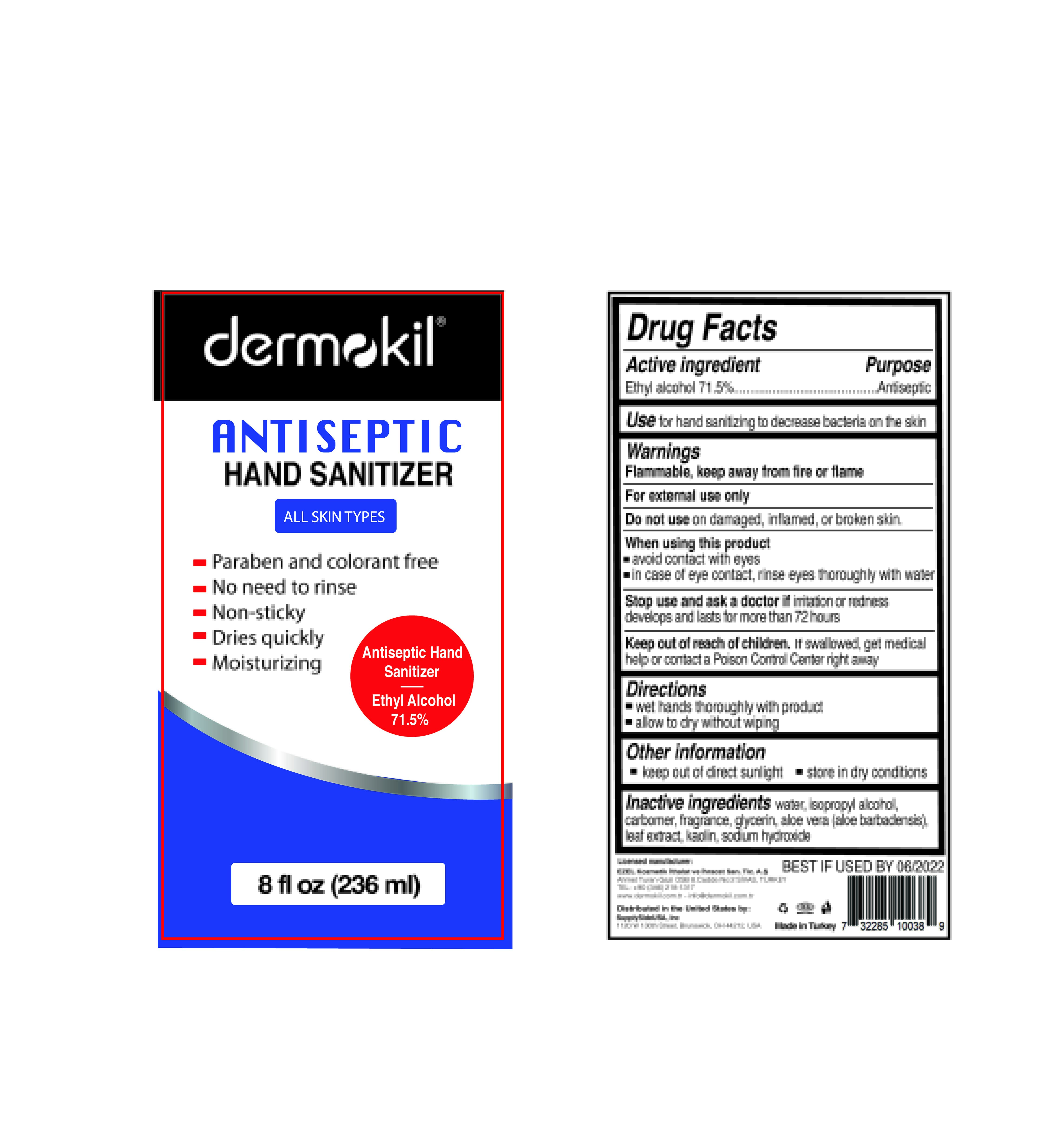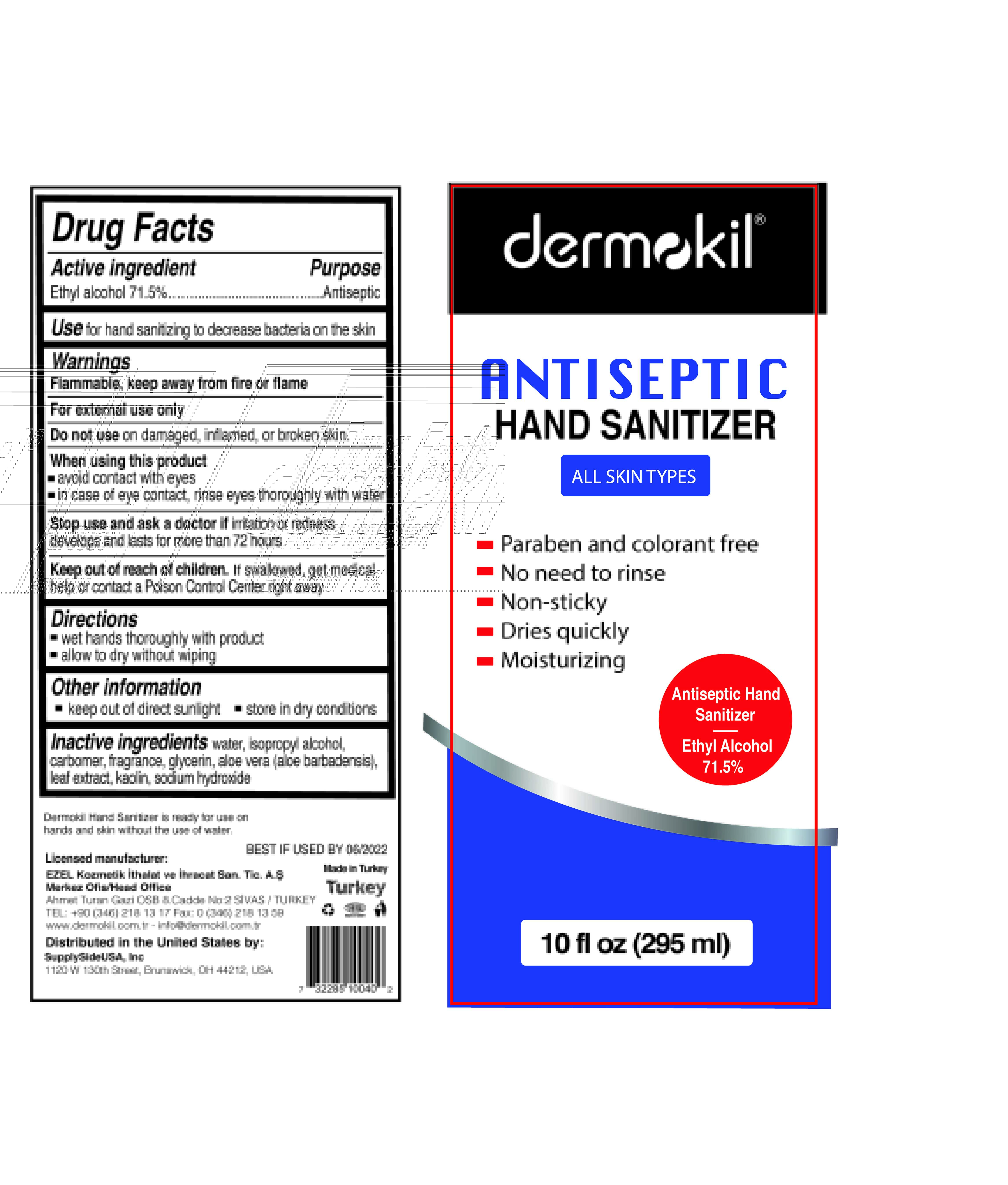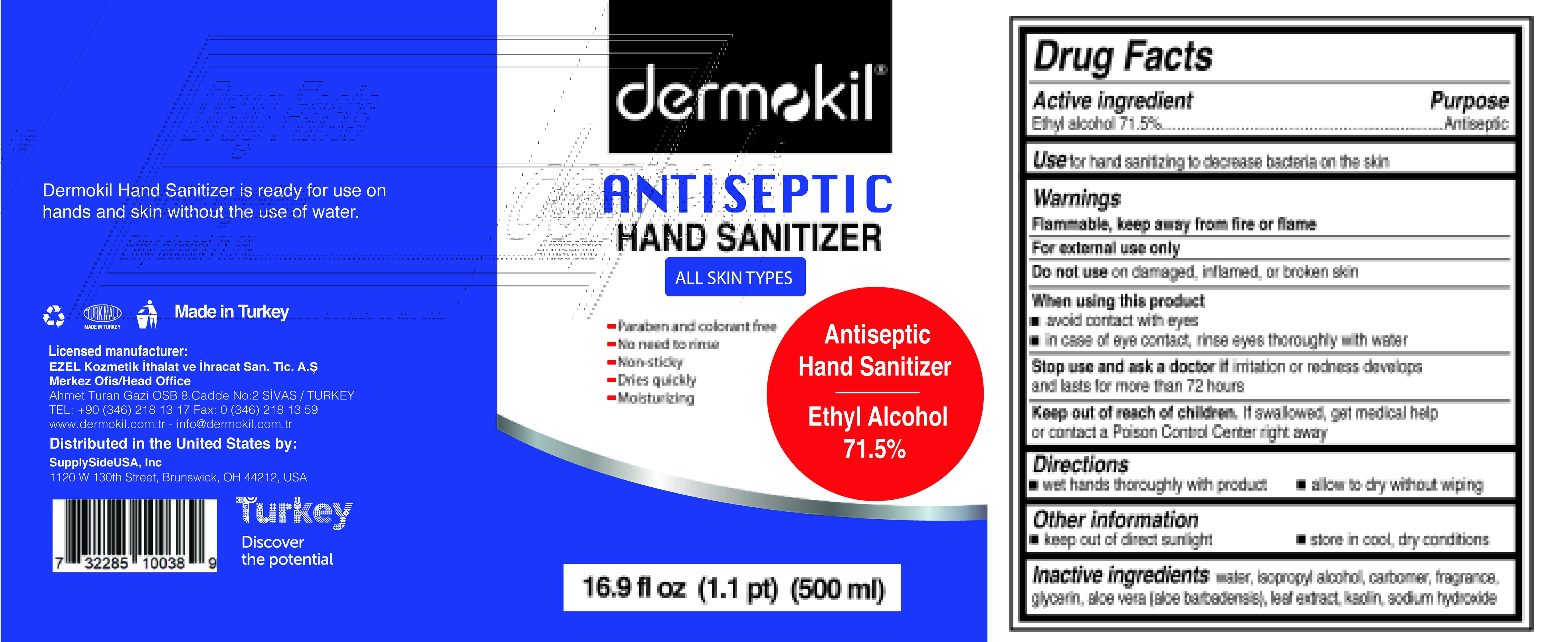 DRUG LABEL: Dermokil
NDC: 75801-786 | Form: GEL
Manufacturer: EZEL KOZMETIK ITH. VE IHR. TIC. VE SAN. A.Ş.
Category: otc | Type: HUMAN OTC DRUG LABEL
Date: 20200821

ACTIVE INGREDIENTS: ALCOHOL 71.5 mL/100 mL
INACTIVE INGREDIENTS: CARBOMER 940; ALOE VERA LEAF POLYSACCHARIDES; SODIUM HYDROXIDE 0.01 mL/100 mL; ISOPROPYL ALCOHOL 2 mL/100 mL; GLYCERIN; WATER; KAOLIN

This is a hand sanitizer manufactured according to the FDA OTC monograph:

1. Alcohol (ethanol) (USP or Food Chemical Codex (FCC) grade) (71.5%, volume/volume (v/v)) in an aqueous solution denatured according to Alcohol and Tobacco Tax and Trade Bureau regulations in 27 CFR part 20.
2. Glycerol
3. Isopropyl alcohol 2% (v/v)
4. Water
5. Sodium hydroxide 0.01% (v/v)

The firm does not add other active or inactive ingredients. Different or additional ingredients may impact the quality and potency of the product.

Active Ingredient(s)

Alcohol 71.5% v/v. Purpose: Antiseptic

Purpose

Antiseptic, Hand Sanitizer

Use

Hand Sanitizer to help reduce bacteria that potentially can cause disease. For use when soap and water are not available.

Warnings

For external use only. Flammable. Keep away from heat or flame

Do not use

- on children less than 2 months age
- on open skin wounds

When using this product keep out of eyes, ears, and mouth. In case of contact with eyes, rinse eyes thoroughly with water.
Stop use and ask a doctor if irritation or rash occurs. These may be signs of a serious condition.
Keep out of reach of children. If swallowed, get medical help or contact a Poison Control Center right away.

Stop use and ask a doctor if irritation or rash occurs. These may be signs of a serious condition.

Keep out of reach of children. If swallowed, get medical help or contact a Poison Control Center right away.

Directions

- Place enough product on hands to cover all surfaces. Rub hands together until dry.
- Supervise children under 6 years of age when using this product to avoid swallowing.

Other information

- Store between 15-30C (59-86F)
- Avoid freezing and excessive heat above 40C (104F)

Inactive ingredients

Aloe barbadensis (aloe vera) leaf extract, carbomer, fragrance, glycerin, isopropyl alcohol, kaolin, sodium hydroxide, water

Package Label - Principal Display Panel

3785 mL NDC: 75801-786-37